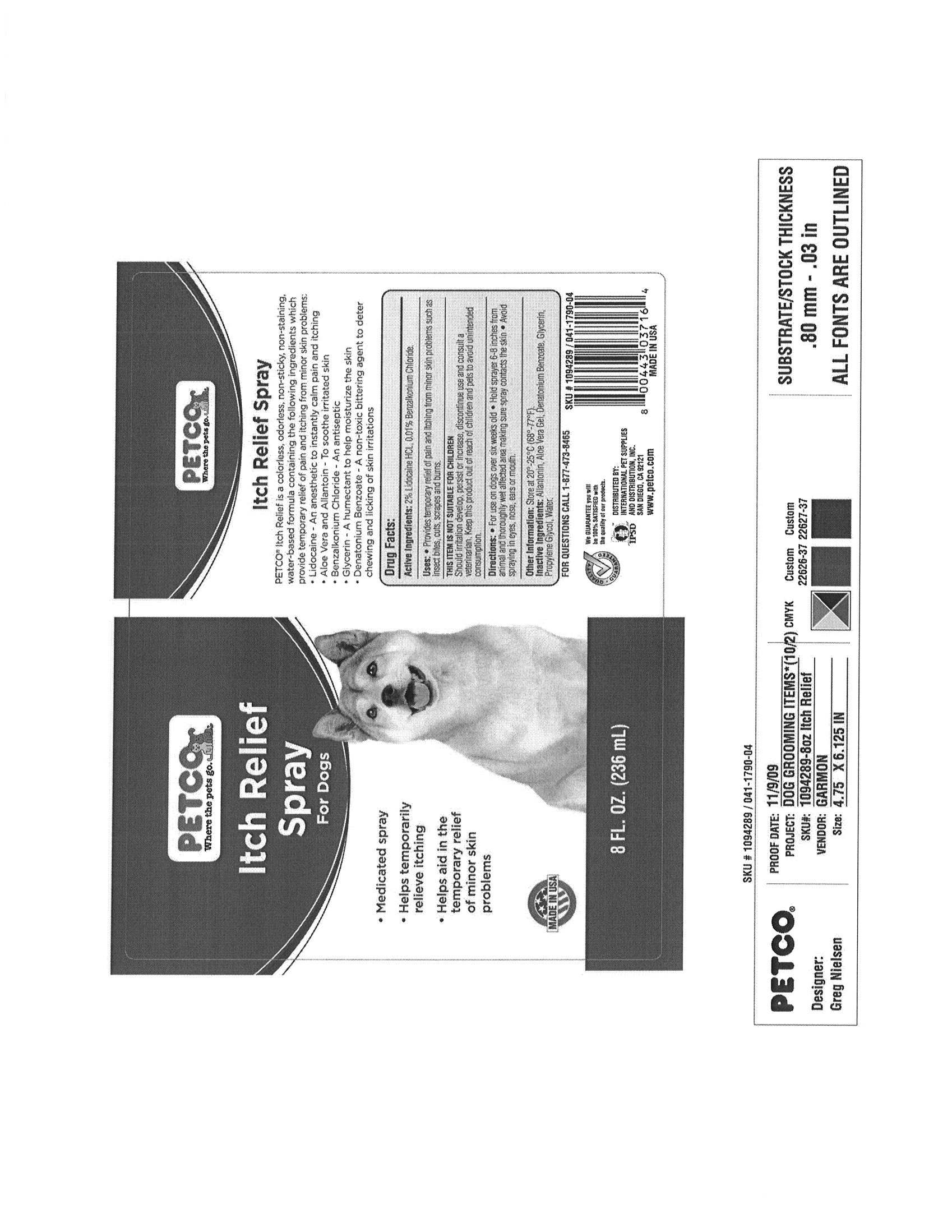 DRUG LABEL: PETCO
NDC: 27102-806 | Form: LIQUID
Manufacturer: PETCO
Category: animal | Type: OTC ANIMAL DRUG LABEL
Date: 20100302

ACTIVE INGREDIENTS: LIDOCAINE HYDROCHLORIDE 4.72 g/236 g
INACTIVE INGREDIENTS: Water; GLYCERIN; ALOE VERA LEAF; ALLANTOIN; DENATONIUM BENZOATE; BENZALKONIUM CHLORIDE

Drug Facts

DESCRIPTION

PETCO

Itch Relief Spray

PETCO Itch Relief is a colorless, odorless, non-sticky, non-staining, water based formula containing the following ingredients which provide temporary relief of pain and itching from minor skin problems:

- Lidocaine - An anesthectic to instantly calm pain and itching
- Aloe Vera and Allantoin - To soothe irritated skin
- Glycerin - A humectant to help moisturize the skin
- Denatonium Benzoate - A non-toxic bittering agent to deter chewing and licking of skin irritations

Active Ingredients

2% Lidocaine HCL, 0.01% Benzalkonium Chloride

Uses

Provides temporary relief of pain and itching from minor skin problems such as insect bites, cuts, scrapes, and burns.

Warnings

Should irritation develop, persist or increase, discontinue use and consult a veterinarian. Keep this product out of reach of children and pets to avoid unintended consumption.

Directions

For use on dogs over six weeks old. Hold sprayer 6-8 inches from animal and thoroughly wet affected area making sure spray contacts the skin. Avoid spraying in eyes, nose, ears or mouth.

other Information

Store at 20-25C (68-77F)

Inactive Ingredients

Water, glycerin, Aloe Vera, Allantoin, Denatonium Benzoate.

FOR QUESTIONS CALL 1-877-473-8465

PACKAGE LABEL

PETCO
Itch Relief
Spray
For Dogs

- Medicated Spray
- Helpstemporarily relieve itching
- Helps aid in the temporary relief of minor skin problems

Veterinarian Approved
NET 8 FL. OZ. (236mL)